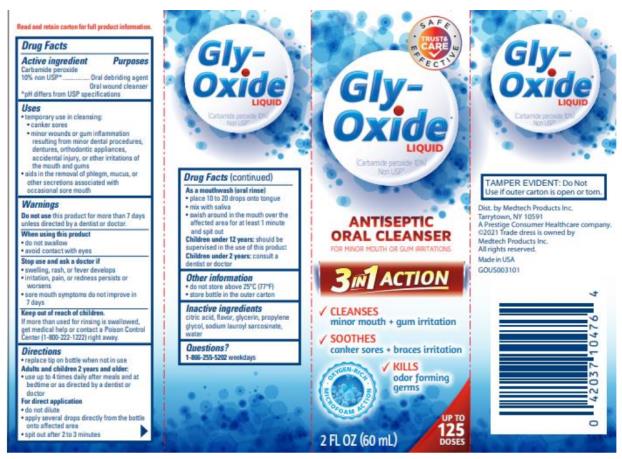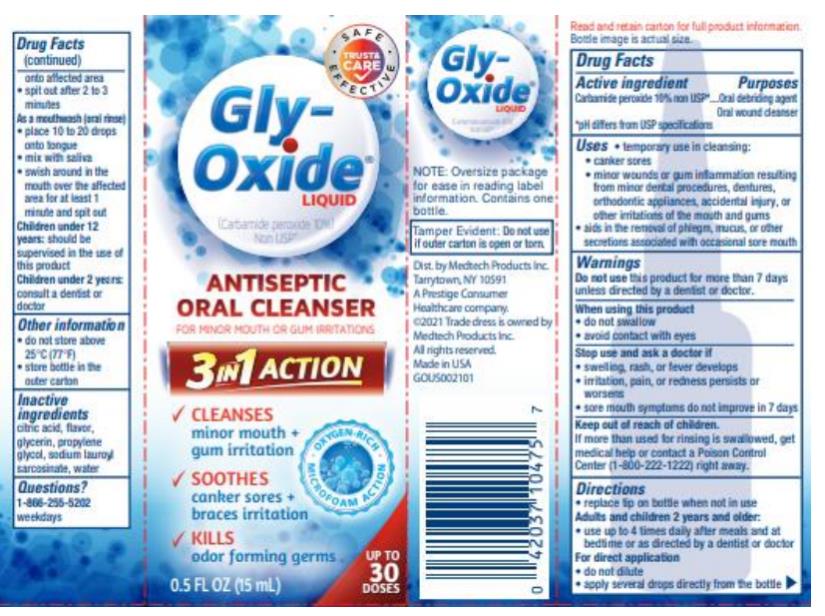 DRUG LABEL: Gly-Oxide
NDC: 63029-500 | Form: LIQUID
Manufacturer: Medtech Products Inc.
Category: otc | Type: HUMAN OTC DRUG LABEL
Date: 20241025

ACTIVE INGREDIENTS: CARBAMIDE PEROXIDE 100 mg/1 mL
INACTIVE INGREDIENTS: CITRIC ACID MONOHYDRATE; GLYCERIN; PROPYLENE GLYCOL; SODIUM LAUROYL SARCOSINATE; WATER

Gly-Oxide

Drug Facts

Active ingredient

Carbamide peroxide 10% non USP*

*pH differs from USP specifications

Purposes

Oral debriding agent

Oral wound cleanser

Uses

- temporary use in cleansing:
  - canker sores
  - minor wounds or gum inflammation resulting from minor dental procedures, dentures, orthodontic appliances, accidental injury, or other irritations of the mouth and gums
- aids in the removal of phlegm, mucus, or other secretions associated with occasional sore mouth

Warnings

Do not use

this product for more than 7 days unless directed by a dentist or doctor.

When using this product

- do not swallow
- avoid contact with eyes

Stop use and ask a doctor if:

- swelling, rash or fever develops
- irritation, pain, or redness persists or worsens
- sore mouth symptoms do not improve in 7 days

Keep out of the reach of children.

If more than used for rinsing is swallowed, get medical help or contact a Poison Control Center (1-800-222-1222) right away.

Directions

- replace tip on bottle when not in use

Adults and children 2 years and older:

- use up to 4 times daily after meals and at bedtime or as directed by a dentist or doctor

For direct application

- do not dilute
- apply several drops directly from the bottle onto affected area
- spit out after 2 to 3 minutes

As a mouthwash (oral rinse)

- place 10 to 20 drops onto tongue
- mix with saliva
- swish around in the mouth over the affected area for at least 1 minute and spit out

Children under 12 years: should be supervised in the use of this product

Children under 2 years: consult a dentist or doctor

Other information

- do not store above 25°C (77°F)
- store bottle in the outer carton

Inactive ingredients

citric acid, flavor, glycerin, propylene glycol, sodium lauroyl sarcosinate, water

Questions?

1-866-255-5202 weekdays

PRINCIPAL DISPLAY PANEL

Gly-Oxide LIQUID
(Carbamide peroxide 10%) Non USP*
ANTISEPTIC ORAL CLEANSER
2FL OZ (60 mL)

PRINCIPAL DISPLAY PANEL

Gly-Oxide LIQUID
(Carbamide peroxide 10%) Non USP*
ANTISEPTIC ORAL CLEANSER
0.5 FL OZ (15 mL)